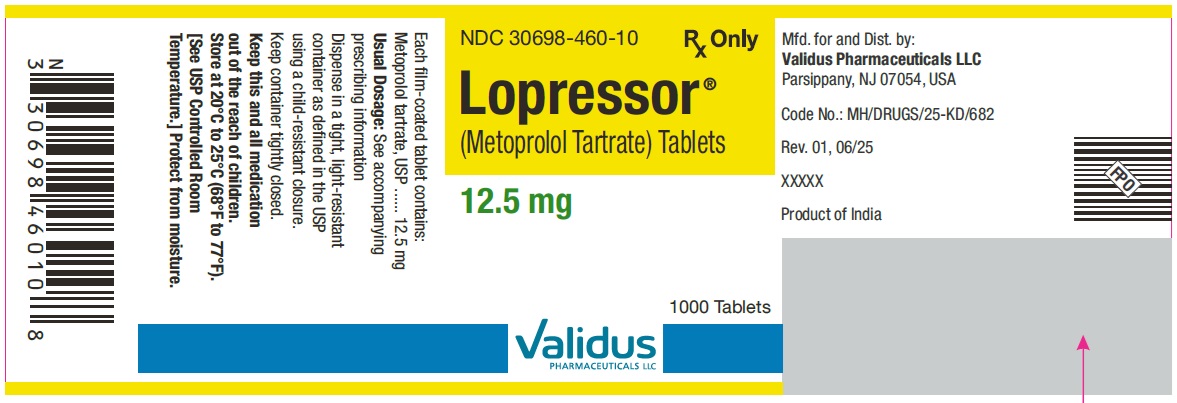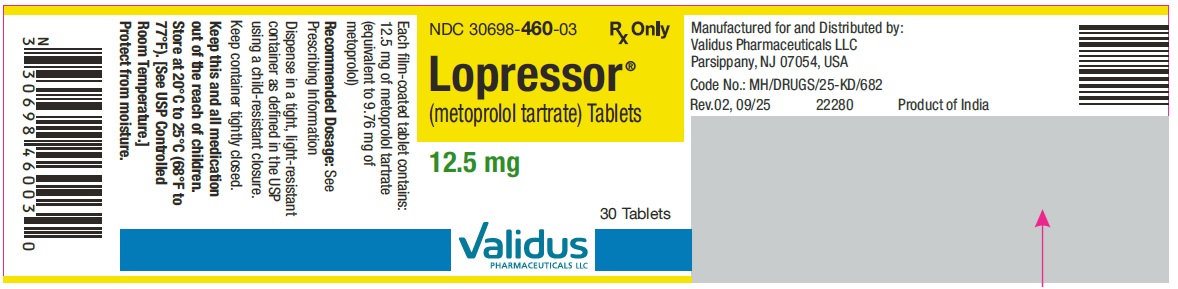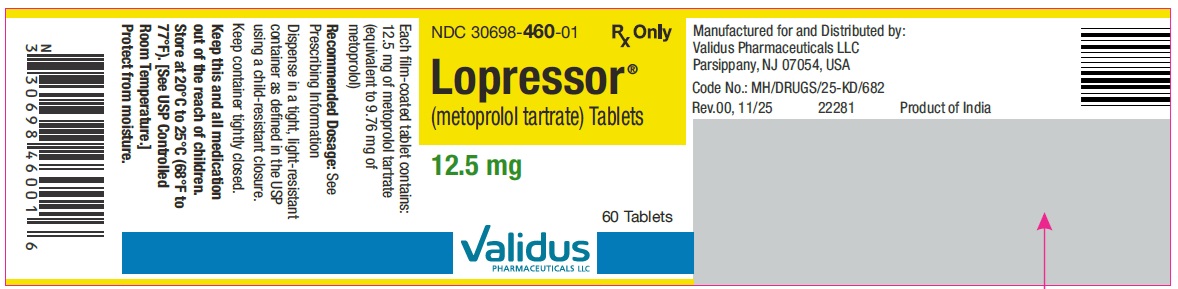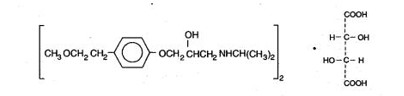 DRUG LABEL: LOPRESSOR
NDC: 30698-460 | Form: TABLET
Manufacturer: VALIDUS PHARMACEUTICALS LLC
Category: prescription | Type: HUMAN PRESCRIPTION DRUG LABEL
Date: 20260126

ACTIVE INGREDIENTS: METOPROLOL TARTRATE 12.5 mg/1 1
INACTIVE INGREDIENTS: SILICON DIOXIDE; LACTOSE MONOHYDRATE; MAGNESIUM STEARATE; MICROCRYSTALLINE CELLULOSE; SODIUM STARCH GLYCOLATE TYPE A POTATO; D&C RED NO. 30; HYPROMELLOSE, UNSPECIFIED; POLYETHYLENE GLYCOL, UNSPECIFIED; TALC; TITANIUM DIOXIDE

HIGHLIGHTS OF PRESCRIBING INFORMATION

These highlights do not include all the information needed to use LOPRESSOR®safely and effectively. See full prescribing information for LOPRESSOR®TABLETS.
LOPRESSOR®(metoprolol tartrate) tablets, for oral use
Initial U.S. Approval: 1992

1 INDICATIONS AND USAGE

LOPRESSOR is a beta-adrenergic blocker indicated in the treatment of hemodynamically stable adult patients with myocardial infarction, to reduce the risk of cardiovascular mortality. (1.1)

2 DOSAGE AND ADMINISTRATION

Myocardial Infarction: The recommended starting dosage is 50 mg orally every 6 hours. Maintenance dosage depends upon hemodynamic tolerance, see full prescribing information. (2.1)

3 DOSAGE FORMS AND STRENGTHS

Tablets: 12.5 mg. of metoprolol tartrate (3)

4 CONTRAINDICATIONS

- Severe bradycardia: Greater than first degree heart block, or sick sinus syndrome without a pacemaker. (4)
- Cardiogenic shock or decompensated heart failure. (4)
- Known hypersensitivity to product components. (4)

5 WARNINGS AND PRECAUTIONS

- Abrupt cessation may exacerbate myocardial ischemia. (5.1)
- Heart Failure: Worsening cardiac failure may occur. (5.2)
- Bronchospastic Disease: Avoid beta-blockers. (5.3)
- Pheochromocytoma: Initiate therapy with an alpha blocker. (5.4)
- Major Surgery: Avoid initiation of high-dose metoprolol in patients undergoing non- cardiac surgery. Do not routinely withdraw chronic beta-blocker therapy prior to surgery. (5.5, 6.1)
- Diabetes: May mask symptoms of hypoglycemia. (5.6)
- Thyrotoxicosis: Abrupt withdrawal in patients with thyrotoxicosis might precipitate a thyroid storm. (5.7)
- Peripheral Vascular Disease: Can aggravate symptoms of arterial insufficiency. (5.9)

6 ADVERSE REACTIONS

- Most common adverse reactions in the setting of treatment of myocardial infarction are hypotension and bradycardia. (6.1)

To report SUSPECTED ADVERSE REACTIONS, contact Validus Pharmaceuticals LLC at 1-866-982-5438 or FDA at 1-800-FDA-1088 or www.fda.gov/medwatch.

7 DRUG INTERACTIONS

- Catecholamine-depleting drugs may have an additive effect when given with beta-blocking agents. (7.1)
- Patients may be unresponsive to the usual doses of epinephrine used to treat allergic reaction. (7.2)
- CYP2D6 Inhibitors are likely to increase metoprolol concentration. (7.3)
- Concomitant use of glycosides, clonidine, and diltiazem and verapamil with beta-blockers can increase the risk of bradycardia. (7.4)
- Beta-blockers including metoprolol, may exacerbate the rebound hypertension that can follow the withdrawal of clonidine. (7.4)

8 USE IN SPECIFIC POPULATIONS

- Hepatic Impairment: Consider initiating LOPRESSOR therapy at low doses and gradually increase dosage to optimize therapy, while monitoring closely for adverse events. (8.6)

FULL PRESCRIBING INFORMATION

1 INDICATIONS AND USAGE

1.1 Myocardial Infarction

LOPRESSOR is indicated in the treatment of hemodynamically stable adult patients with myocardial infarction (MI) to reduce cardiovascular mortality.

2 DOSAGE AND ADMINISTRATION

2.1 Myocardial Infarction

The recommended starting dose in hemodynamically stable patients is 50 mg orally every 6 hours. In case of intolerance, reduce the starting dose to 25 mg orally every 6 hours and administer for 48 hours. Titrate dosage based on tolerability and hemodynamic parameters (i.e., heart rate, blood pressure). LOPRESSOR should preferably be administered with or following meals. The maximum daily maintenance dosage is 100 mg orally twice daily.

3 DOSAGE FORMS AND STRENGTHS

LOPRESSOR is supplied as a 12.5 mg tablet that is pink-colored, film coated, round, biconvex, debossed with “˄E” on one side, and plain on the other side.

4 CONTRAINDICATIONS

LOPRESSOR is contraindicated in severe bradycardia, second or third degree heart block, cardiogenic shock, systolic blood pressure <100, decompensated heart failure, sick sinus syndrome (unless a permanent pacemaker is in place), and in patients who are hypersensitive to any component of this product.

5 WARNINGS AND PRECAUTIONS

5.1 Abrupt Cessation of Therapy

Following abrupt cessation of therapy with certain beta-blocking agents, exacerbations of angina pectoris and, in some cases, myocardial infarction have occurred. When discontinuing chronically administered LOPRESSOR, gradually reduce the dosage over a period of 1 to 2 weeks and monitor the patient. Warn patients not to interrupt therapy without their physician’s advice.

5.2 Heart Failure

Worsening cardiac failure may occur during up-titration of LOPRESSOR. If such symptoms occur, increase diuretics and restore clinical stability before advancing the dose of LOPRESSOR [see Dosage and Administration (2)]. It may be necessary to lower the dose of LOPRESSOR or temporarily discontinue it. Such episodes do not preclude subsequent successful titration of LOPRESSOR.

5.3 Bronchospastic Disease

Patients with bronchospastic disease, should in general, not receive beta-blockers, including LOPRESSOR. Because of its relative beta1cardio-selectivity, however, LOPRESSOR may be used in patients with bronchospastic disease who do not respond to, or cannot tolerate, other antihypertensive treatment. Because beta1-selectivity is not absolute, use the lowest possible dose of LOPRESSOR. Bronchodilators, including beta2-agonists, should be readily available or administered concomitantly [see Dosage and Administration (2)].

5.4 Pheochromocytoma

If LOPRESSOR is used in the setting of pheochromocytoma, it should be given in combination with an alpha blocker, and only after the alpha blocker has been initiated. Administration of beta-blockers alone in the setting of pheochromocytoma has been associated with a paradoxical increase in blood pressure due to the attenuation of beta-mediated vasodilatation in skeletal muscle.

5.5 Major Surgery

Avoid initiation of a high-dose regimen of beta blocker therapy in patients undergoing non-cardiac surgery, since such use in patients with cardiovascular risk factors has been associated with bradycardia, hypotension, stroke and death.

Chronically administered beta-blocking therapy should not be routinely withdrawn prior to major surgery, however, the impaired ability of the heart to respond to reflex adrenergic stimuli may augment the risks of general anesthesia and surgical procedures.

5.6 Hypoglycemia

Beta-blockers may prevent early warning signs of hypoglycemia, such as tachycardia, and increase the risk for severe or prolonged hypoglycemia at any time during treatment, especially in patients with diabetes mellitus or children and patients who are fasting (i.e., surgery, not eating regularly, or are vomiting). If severe hypoglycemia occurs, patients should be instructed to seek emergency treatment.

5.7 Thyrotoxicosis

Beta-adrenergic blockade may mask certain clinical signs of hyperthyroidism, such as tachycardia. Abrupt withdrawal of beta-blockade may precipitate a thyroid storm.

5.8 Risk of Anaphylactic Reactions

While taking beta-blockers, patients with a history of severe anaphylactic reaction to a variety of allergens may be more reactive to repeated challenge, either accidental, diagnostic, or therapeutic. Such patients may be unresponsive to the usual doses of epinephrine used to treat allergic reaction.

5.9 Peripheral Vascular Disease

Beta-blockers can precipitate or aggravate symptoms of arterial insufficiency in patients with peripheral vascular disease.

6 ADVERSE REACTIONS

The following adverse reactions are described elsewhere in labeling:

- Worsening Ischemia with Abrupt Discontinuation [see Warnings and Precautions (5)]
- Worsening heart failure [see Warnings and Precautions (5)].
- Worsening atrioventricular (AV) block [see Contraindications (4)].

6.1 Clinical Trials Experience

Because clinical trials are conducted under widely varying conditions, adverse reaction rates observed in the clinical trials of a drug cannot be directly compared to rates in the clinical trials of another drug and may not reflect the rates observed in practice.

Myocardial Infarction

In a randomized comparison of LOPRESSOR and placebo in the setting of acute MI [see Clinical studies 14.1] the following adverse reactions were reported:

Adverse Reaction | LOPRESSOR N=698 % | Placebo N=697 %
Hypotension (systolic BP < 90 mm Hg) | 27.4% | 23.2%
Bradycardia (heart rate < 40 beats/min) | 15.9% | 6.7%
Second- or third-degree heart block | 4.7% | 4.7%
First-degree heart block (P-R ≥ 0.26 sec) | 5.3% | 1.9%
Heart failure | 27.5% | 29.6%

6.2 Post-Marketing Experience

The following adverse reactions have been reported during post-approval use of LOPRESSOR. Because these reactions are reported voluntarily from a population of uncertain size, it is not always possible to reliably estimate their frequency or establish a causal relationship to drug exposure.

Central Nervous System:Reversible mental depression progressing to catatonia; an acute reversible syndrome characterized by disorientation for time and place, short-term memory loss, emotional lability, slightly clouded sensorium, and decreased cognitive performance.

Cardiovascular: Worsening AV block [see Contraindications (4)].

Hematologic:Agranulocytosis, nonthrombocytopenic purpura and thrombocytopenic purpura.

Hypersensitive Reactions:Fever combined with aching and sore throat, laryngospasm and respiratory distress.

Laboratory Findings:

Increase in blood triglycerides, elevated transaminase and decrease in high-density lipoprotein (HDL)

7 DRUG INTERACTIONS

7.1 Catecholamine Depleting Drugs

Observe patients treated with LOPRESSOR plus a catecholamine depletor for evidence of hypotension or marked bradycardia, which may produce vertigo, syncope, or postural hypotension. Catecholamine depleting drugs (e.g., reserpine, monoamine oxidase (MAO) inhibitors) may have an additive effect when given with beta-blocking agents.

7.2 Epinephrine

The cardiostimulating and bronchodilating effects of epinephrine are antagonized by beta-adrenergic blocking drugs, such as metoprolol. Higher doses of epinephrine might be necessary for patients taking metoprolol.

7.3 CYP2D6 Inhibitors

Monitor patients closely when the combination use of CYP2D6 inhibitor and metoprolol cannot be avoided. Drugs that are strong inhibitors of CYP2D6 such as quinidine, fluoxetine, paroxetine, and propafenone were shown to double metoprolol concentrations. While there is no information about moderate or weak inhibitors, these may also increase metoprolol concentration. Increases in plasma concentration decrease the beta1cardioselectivity of metoprolol [see Clinical Pharmacology (12.3)] .

7.4 Negative Chronotropes

If clonidine and metoprolol are coadministered, withdraw the beta-blocker several days before the gradual withdrawal of clonidine because metoprolol may exacerbate the rebound hypertension that can follow the withdrawal of clonidine. If replacing clonidine with metoprolol, delay the introduction of metoprolol for several days after clonidine discontinuation.

Digitalis glycosides, clonidine, diltiazem, and verapamil slow atrioventricular conduction and decrease heart rate. Concomitant use with beta blockers can increase the risk of bradycardia.

8 USE IN SPECIFIC POPULATIONS

8.1 Pregnancy

Risk Summary

Available data from published observational studies have not demonstrated an association of adverse developmental outcomes with maternal use of metoprolol during pregnancy (see Data) . Untreated myocardial infarction during pregnancy can lead to adverse outcomes for the mother and the fetus (see Clinical Considerations) . In animal reproduction studies, metoprolol has been shown to increase post- implantation loss and decrease neonatal survival in rats at oral dosages of 500 mg/kg/day, approximately 11 times the daily dose of 450 mg in a 60-kg patient on a mg/m^2basis.

All pregnancies have a background risk of birth defect, loss, or other adverse outcomes. The estimated background risk of major birth defects and miscarriage for the indicated population is unknown. In the U.S. general population, the estimated background risk of major birth defects and miscarriage in clinically recognized pregnancies is 2 to 4% and 15 to 20%, respectively.

Clinical consideration

Fetal/Neonatal adverse reactions

Metoprolol crosses the placenta. Neonates born to mothers who are receiving metoprolol during pregnancy, may be at risk for hypotension, hypoglycemia, bradycardia, and respiratory depression. Observe neonates and manage accordingly.

Data

Human Data

Data from published observational studies did not demonstrate an association of major congenital malformations and use of metoprolol in pregnancy. The published literature has reported inconsistent findings of intrauterine growth retardation, preterm birth and perinatal mortality with maternal use of metoprolol during pregnancy; however, these studies have methodological limitations hindering interpretation. Methodological limitations include retrospective design, concomitant use of other medications, and other unadjusted confounders that may account for the study findings including the underlying disease in the mother. These observational studies cannot definitively establish or exclude any drug-associated risk during pregnancy.

Animal Data

Metoprolol has been shown to increase post-implantation loss and decrease neonatal survival in rats at oral dosages of 500 mg/kg/day, i.e. 11 times, on a mg/m^2basis, the daily dose of 450 mg in a 60-kg patient.

No fetal abnormalities were observed when pregnant rats received metoprolol orally up to a dose of 200 mg/kg/day, i.e. 4 times, the daily dose of 400mg in a 60-kg patient.

8.2 Lactation

Risk Summary

Limited available data from published literature report that metoprolol is present in human milk. The estimated daily infant dose of metoprolol received from breastmilk ranges from 0.05 mg to less than 1 mg. The estimated relative infant dosage was 0.5% to 2% of the mother's weight-adjusted dosage (see Data). No adverse reactions of metoprolol on the breastfed infant have been identified. There is no information regarding the effects of metoprolol on milk production.

Clinical consideration

Monitoring for adverse reactions

For a lactating woman who is a slow metabolizer of metoprolol, monitor the breastfed infant for bradycardia and other symptoms of beta blockade such as dry mouth, skin or eyes, diarrhea or constipation. In a report of 6 mothers taking metoprolol, none reported adverse effects in her breastfed infant.

Data

Limited published cases estimate the infant daily dose of metoprolol received from breast milk range from 0.05 mg to less than 1 mg.

In 2 women who were taking unspecified amount of metoprolol, milk samples were taken after one dose of metoprolol. The estimated amount of metoprolol and alpha-hydroxymetoprolol in breast milk is reported to be less than 2% of the mother's weight-adjusted dosage.

In a small study, breast milk was collected every 2 to 3 hours over one dosage interval, in three mothers (at least 3 months postpartum) who took metoprolol of unspecified amount. The average amount of metoprolol present in breast milk was 71.5 mcg/day (range 17.0 mcg to 158.7 mcg). The average relative infant dosage was 0.5% of the mother's weight-adjusted dosage.

8.3 Females and Males of Reproductive Potential

Risk Summary

Based on the published literature, beta blockers (including metoprolol) may cause erectile dysfunction and inhibit sperm motility. In animal fertility studies, metoprolol has been associated with reversible adverse effects on spermatogenesis starting at oral dose level of 3.5 mg/kg in rats, which would correspond to a dose of 34 mg/day in humans in mg/m^2 equivalent, although other studies have shown no effect of metoprolol on reproductive performance in male rats.

No evidence of impaired fertility due to metoprolol was observed in rats [see Nonclinical Toxicology (13.1)].

8.4 Pediatric Use

Safety and effectiveness of LOPRESSOR have not been established in pediatric patients.

8.5 Geriatric Use

In worldwide clinical trials of LOPRESSOR in myocardial infarction, where approximately 478 patients were over 65 years of age (0 over 75 years of age), no age-related differences in safety and effectiveness were found. Other reported clinical experience in myocardial infarction has not identified differences in response between the elderly and younger patients.

In general, use a low initial starting dose in elderly patients given their greater frequency of decreased hepatic, renal, or cardiac function, and of concomitant disease or other drug therapy.

8.6 Hepatic Impairment

No studies have been performed with LOPRESSOR in patients with hepatic impairment. LOPRESSOR is metabolized by the liver, metoprolol blood levels are likely to increase substantially with poor hepatic function. Therefore, initiate therapy at doses lower than those recommended; and increase doses gradually in patients with impaired hepatic function.

8.7 Renal Impairment

The systemic availability and half-life of metoprolol in patients with renal failure do not differ to a clinically significant degree from those in normal subjects. No reduction in dosage is needed in patients with renal failure [see Clinical Pharmacology (12.3)] .

10 OVERDOSAGE

Signs and Symptoms - Overdosage of LOPRESSOR may lead to severe bradycardia, hypotension, and cardiogenic shock. Clinical presentation can also include AV block, heart failure, bronchospasm, hypoxia, impairment of consciousness/coma, nausea, and vomiting.

Treatment – Consider treating the patient with intensive care. Patients with myocardial infarction or heart failure may be prone to significant hemodynamic instability. Beta-blocker overdose may result in significant resistance to resuscitation with adrenergic agents, including beta-agonists. On the basis of the pharmacologic actions of metoprolol, employ the following measures.

Hemodialysis is unlikely to make a useful contribution to metoprolol elimination [see Clinical Pharmacology (12.3)] .

Bradycardia: Evaluate the need for atropine, adrenergic-stimulating drugs or pacemaker to treat bradycardia and conduction disorders.

Hypotension: Treat underlying bradycardia. Consider intravenous vasopressor infusion, such as dopamine or norepinephrine.

Heart failure and shock: May be treated when appropriate with suitable volume expansion, injection of glucagon (if necessary, followed by an intravenous infusion of glucagon), intravenous administration of adrenergic drugs such as dobutamine, with α1receptor agonistic drugs added in presence of vasodilation.

Bronchospasm: Can usually be reversed by bronchodilators

11 DESCRIPTION

LOPRESSOR tablets contain metoprolol tartrate, a beta-adrenergic blocker. Metoprolol tartrate is (±)-1- (Isopropylamino)-3-[p-(2-methoxyethyl) phenoxy]-2-propanol L-(+)-tartrate (2:1) salt, and its structural formula is

Metoprolol tartrate USP is a white, practically odorless, crystalline powder with a molecular weight of 684.82 g/mol. It is very soluble in water; freely soluble in methylene chloride, in chloroform, and in alcohol; slightly soluble in acetone; and insoluble in ether.

LOPRESSOR is available as 12.5 mg tablets for oral administration containing 12.5 mg metoprolol tartrate (equivalent to 9.76 mg of metoprolol).

Inactive Ingredients: Tablets contain colloidal silicon dioxide, lactose monohydrate, magnesium stearate, microcrystalline cellulose, sodium starch glycolate. Film coating contains D&C Red 30, hypromellose, polyethylene glycol, talc, and titanium dioxide.

12 CLINICAL PHARMACOLOGY

12.1 Mechanism of Action

Metoprolol is a beta1-selective (cardioselective) adrenergic receptor blocking agent. This preferential effect is not absolute, however, and at higher plasma concentrations, metoprolol also inhibits beta2-adrenoreceptors, chiefly located in the bronchial and vascular musculature.

Metoprolol has no intrinsic sympathomimetic activity, and membrane-stabilizing activity is detectable only at plasma concentrations much greater than required for beta-blockade. Animal and human experiments indicate that metoprolol slows the sinus rate and decreases AV nodal conduction.

The relative beta1-selectivity of metoprolol has been confirmed by the following: (1) In normal subjects, metoprolol is unable to reverse the beta2-mediated vasodilating effects of epinephrine. This contrasts with the effect of nonselective beta-blockers, which completely reverse the vasodilating effects of epinephrine. (2) In asthmatic patients, metoprolol reduces FEV1and FVC significantly less than a nonselective beta-blocker, propranolol, at equivalent beta1-receptor blocking doses.

12.2 Pharmacodynamics

Clinical pharmacology studies have confirmed the beta-blocking activity of metoprolol in humans, as shown by (1) reduction in heart rate and cardiac output at rest and upon exercise, (2) reduction of systolic blood pressure upon exercise, (3) inhibition of isoproterenol-induced tachycardia, and (4) reduction of reflex orthostatic tachycardia.

The relationship between plasma metoprolol levels and reduction in exercise heart rate is independent of the pharmaceutical formulation. Beta1-blocking effects in the range of 30-80% of the maximal effect (approximately 8 to 23% reduction in exercise heart rate) correspond to metoprolol plasma concentrations from 30 to 540 nmol/L. The relative beta1-selectivity of metoprolol diminishes, and blockade of beta2-adrenoceptors increases at plasma concentration above 300 nmol/L.

12.3 Pharmacokinetics

Absorption:The estimated oral bioavailability of immediate release metoprolol is about 50% because of pre- systemic metabolism which is saturable leading to non-proportionate increase in the exposure with increased dose.

Distribution:Metoprolol is extensively distributed with a reported volume of distribution of 3.2 to 5.6 L/kg. About 10% of metoprolol in plasma is bound to serum albumin. Metoprolol is known to cross the placenta and is found in breast milk. Metoprolol is also known to cross the blood brain barrier following oral administration and cerebrospinal fluid (CSF) concentrations close to that observed in plasma have been reported. Metoprolol is not a significant P-glycoprotein substrate.

Elimination:

Elimination of LOPRESSOR is mainly by biotransformation in the liver. The mean elimination half-life of metoprolol is 3 to 4 hours; in poor CYP2D6 metabolizers the half-life may be 7 to 9 hours.

Metabolism:LOPRESSOR is primarily metabolized by CYP2D6. Metoprolol is a racemic mixture of R- and S- enantiomers, and when administered orally, it exhibits stereoselective metabolism that is dependent on oxidation phenotype. CYP2D6 is absent (poor metabolizers) in about 8% of Caucasians and about 2% of most other populations. Poor CYP2D6 metabolizers exhibit several-fold higher plasma concentrations of Metoprolol tartrate than extensive metabolizers with normal CYP2D6 activity thereby decreasing Metoprolol tartrate’s cardioselectivity.

Excretion: Approximately 95% of the dose can be recovered in urine. In most subjects (extensive metabolizers), less than 5% of an oral dose and the rest is excreted by the kidneys as metabolites that appear to have no beta-blocking activity. The renal clearance of the stereoisomers does not exhibit stereo-selectivity in renal excretion.

Specific populations

Geriatric patients:The geriatric population may show slightly higher plasma concentrations of metoprolol as a combined result of a decreased metabolism of the drug in elderly population and a decreased hepatic blood flow. However, this increase is not clinically significant or therapeutically relevant.

Patients with Renal impairment:The systemic availability and half-life of LOPRESSOR in patients with renal failure do not differ to a clinically significant degree from those in normal subjects.

Patients with Hepatic Impairment: Since the drug is primarily eliminated by hepatic metabolism, hepatic impairment may impact the pharmacokinetics of metoprolol.

Drug Interactions:

Metoprolol is metabolized predominantly by CYP2D6. In healthy subjects with CYP2D6 extensive metabolizer phenotype, coadministration of quinidine 100 mg, a potent CYP2D6 inhibitor, and immediate-release metoprolol 200 mg tripled the concentration of S-metoprolol and doubled the metoprolol elimination half-life. In four patients with cardiovascular disease, coadministration of propafenone 150 mg t.i.d. with immediate-release metoprolol 50 mg t.i.d. increased the steady-state metoprolol concentration 2- to 5-fold compared to metoprolol alone. Extensive metabolizers who concomitantly use CYP2D6 inhibiting drugs will have increased (several-fold) metoprolol blood levels, decreasing metoprolol's cardioselectivity [see Drug Interactions (7.2)].

12.5 Pharmacogenomics

CYP2D6 is absent in about 8% of Caucasians (poor metabolizers) and about 2% of most other populations. CYP2D6 can be inhibited by several drugs. Poor metabolizers of CYP2D6 will have increased (several-fold) metoprolol blood levels, decreasing metoprolol's cardioselectivity.

13 NONCLINICAL TOXICOLOGY

13.1 Carcinogenesis, Mutagenesis, Impairment of Fertility

Long-term studies in animals have been conducted to evaluate the carcinogenic potential of metoprolol tartrate. In 2-year studies in rats at three oral dosage levels of up to 800 mg/kg/day (19 times, on a mg/m^2basis, the daily dose of 400 mg for a 60-kg patient), there was no increase in the development of spontaneously occurring benign or malignant neoplasms of any type. The only histologic changes that appeared to be drug related were an increased incidence of generally mild focal accumulation of foamy macrophages in pulmonary alveoli and a slight increase in biliary hyperplasia. In a 21-month study in Swiss albino mice at three oral dosage levels of up to 750 mg/kg/day (9 times, on a mg/m^2basis, the daily dose of 400 mg for a 60-kg patient), benign lung tumors (small adenomas) occurred more frequently in female mice receiving the highest dose than in untreated control animals. There was no increase in malignant or total (benign plus malignant) lung tumors, nor in the overall incidence of tumors or malignant tumors. This 21-month study was repeated in CD-1 mice, and no statistically or biologically significant differences were observed between treated and control mice of either sex for any type of tumor.

All genotoxicity tests performed on metoprolol tartrate (a dominant lethal study in mice, chromosome studies in somatic cells, a Salmonella/mammalian-microsome mutagenicity test, and a nucleus anomaly test in somatic interphase nuclei) and metoprolol succinate (a Salmonella/mammalian-microsome mutagenicity test) were negative.

No evidence of impaired fertility due to metoprolol tartrate was observed in a study performed in rats at doses up to 55.5 times, on a mg/m^2basis, the daily dose of 450 mg in a 60-kg patient.

14 CLINICAL STUDIES

14.1 Myocardial Infarction

The study supporting the approval of metoprolol post-myocardial infarction to reduce cardiovascular mortality was conducted before the reperfusion era. In this double-blind, placebo-controlled study, 1395 patients with suspected acute myocardial infarction were randomized to LOPRESSOR or placebo. LOPRESSOR reduced 3-month cardiovascular mortality by 36%.

Patients were randomized and treated as soon as possible after arrival in the hospital, once their clinical condition had stabilized and their hemodynamic status had been carefully evaluated. Subjects were ineligible if they had hypotension, bradycardia, peripheral signs of shock, and/or more than minimal basal rales as signs of congestive heart failure. Initial treatment consisted of intravenous followed by oral administration of LOPRESSOR or placebo, given in a coronary care or comparable unit. Oral maintenance therapy with LOPRESSOR or placebo was continued for 3 months. The median delay from the onset of symptoms to the initiation of therapy was 8 hours in both the LOPRESSOR - and placebo-treatment groups. Among patients treated with LOPRESSOR, there were comparable reductions in 3- month cardiovascular mortality for those treated early (≤ 8 hours) and those in whom treatment was started later. Significant reductions in the incidence of ventricular fibrillation and in chest pain following initial intravenous therapy were also observed with LOPRESSOR and were independent of the interval between onset of symptoms and initiation of therapy.

16 HOW SUPPLIED/ STORAGE AND HANDLING

LOPRESSOR (metoprolol tartrate) tablets

Tablets 12.5 mg- pink colored film coated, round, biconvex tablets debossed with “˄E” on one side and plain on the other side. They are available as follows:

Bottles of 30 ………………………………………..NDC 30698-460-03

Bottles of 60 ………………………………………..NDC 30698-460-01

Bottles of 1,000 …………………………………….NDC 30698-460-10

Storage:

Store at 20°C to 25°C (68°F to 77°F). [See USP Controlled Room Temperature.]

Protect from moisture.

Dispense in a tight, light-resistant container as defined in the USP using a child-resistant closure.

17 PATIENT COUNSELING INFORMATION

Advise patients to take LOPRESSOR regularly and continuously, as directed, preferably with or immediately following meals. If a dose is missed, the patient should take only the next scheduled dose (without doubling it). Patients should not interrupt or discontinue LOPRESSOR without consulting the physician.

Advise patients (1) to avoid operating automobiles and machinery or engaging in other tasks requiring alertness until the patient’s response to therapy with LOPRESSOR has been determined; (2) to contact the physician if any difficulty in breathing occurs; (3) to inform the physician or dentist before any type of surgery that he or she is taking LOPRESSOR.

Inform patients or caregivers that there is a risk of hypoglycemia when LOPRESSOR is given to patients who are fasting or who are vomiting. Instruct patients or caregivers how to monitor for signs of hypoglycemia [see Warnings and Precautions (5.6)].

Manufactured for and Distributed by:
Validus Pharmaceuticals LLC
Parsippany, NJ 07054, USA
info@validuspharma.com
www.validuspharma.com

Revised: 01, 11/2025

PACKAGE LABEL.PRINCIPAL DISPLAY PANEL

Lopressor®(metoprolol tartrate) Tablets, USP 12.5 mg - NDC 30698-460-03 - 30s Bottle Label

Lopressor®(metoprolol tartrate) Tablets, USP 12.5 mg - NDC 30698-460-01 - 60s Bottle Label

Lopressor®(metoprolol tartrate) Tablets, USP 12.5 mg - NDC 30698-460-10 - 1,000s Bottle Label